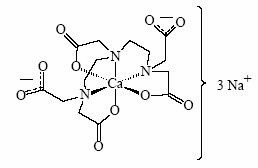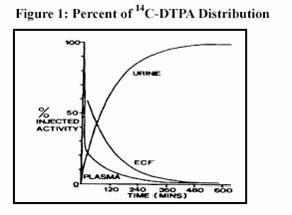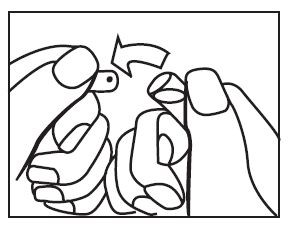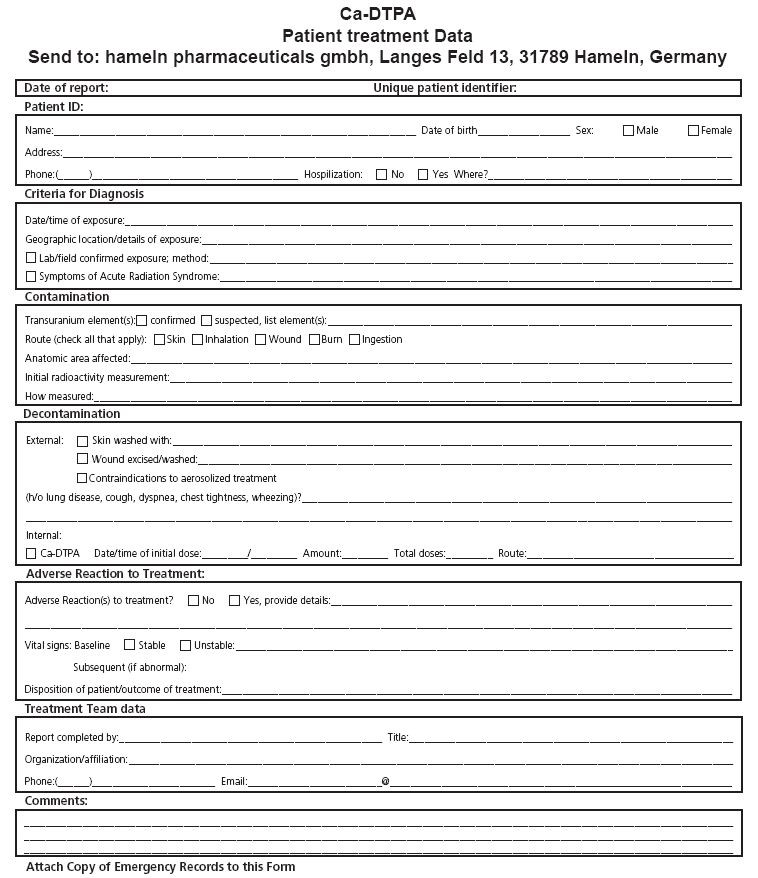 DRUG LABEL: Unknown
Manufacturer: Hameln Pharmaceuticals
Category: prescription | Type: HUMAN PRESCRIPTION DRUG LABELING
Date: 20061218

Pentetate calcium trisodium injection

1000 mg

For Intravenous or Inhalation Administration

Package Insert - Instruction for Use

DESCRIPTION

Pentetate calcium trisodium injection contains the sodium salt of calcium diethylenetriaminepentaacetate. Pentetate calcium trisodium is also known as trisodium calcium diethylenetriaminepentaacetate and is commonly referred to as Ca-DTPA. It has a molecular formula of Na3CaC14H18N3O10 and a molecular weight of 497.4 Daltons. It is represented by the following structural formula:

Ca-DTPA is supplied as a clear, colorless, hyperosmolar (1260 mOsmol/kg) solution in a colorless ampoule containing 5 mL. The ampoule contents are sterile, non-pyrogenic and suitable for intravenous administration. Each mL of solution contains the equivalent of 200 mg pentetate calcium trisodium (obtained from 158.17 mg pentetic acid, 40.24 mg calcium carbonate and NaOH) in water for injection, USP. The pH of the solution is adjusted with NaOH and is between 7.3 - 8.3.

CLINICAL PHARMACOLOGY

General

Ca-DTPA forms stable chelates with metal ions by exchanging calcium for a metal of greater binding capacity. The radioactive chelates are then excreted by glomerular filtration into the urine. In animal studies, Ca-DTPA forms less stable chelates with uranium and neptunium in vivo resulting in the deposition of these elements in tissues including the bone. Ca-DTPA treatments are not expected to be effective for uranium and neptunium. Radioactive iodine is not bound by DTPA.

Pharmacodynamics

In a study of rodents internally contaminated with plutonium, the rate of plutonium elimination was measured after treatment with Ca-DTPA and Zn-DTPA given intravenously as a single dose of 10 to 1,000 µmol/kg (0.54 – 54 × maximum human dose, MHD). When treated within one hour of internal contamination, Ca-DTPA resulted in about a 10-fold higher rate of elimination of plutonium in the urine as compared to Zn-DTPA. The chelating capacity of Ca-DTPA is greatest immediately and up to approximately 24 hours after internal contamination when the radiocontaminant is still circulating and readily available for chelation. After the first dose of Ca-DTPA, maintenance treatment with either Ca-DTPA or Zn-DTPA resulted in similar rates of elimination of radioactivity. However, at comparable doses, Ca-DTPA had more toxicity (e.g., more depletion of trace metals, higher rate of mortality, the presence of kidney and liver vacuolization, and small bowel hemorrhagic lesions).

In another study, rodents contaminated with aerosolized plutonium and americium were treated with Ca-DTPA and Zn-DTPA. The treatment schedule involved inhalation of Ca-DTPA 2 µmol/kg (0.11 MHD) 30 minutes after contamination followed by inhalation of Zn-DTPA 2 µmol/kg at approximately 6 hours, 1, 2, 3, and 6 days, then twice weekly to day 26 or day 27. The treatment regime reduced the lung deposit of plutonium and americium to 1-2% of that in untreated animals. Systemic deposit in liver and skeleton were reduced by half.

Literature and U.S. Registry data in humans indicate that intravenous administration of Ca-DTPA forms chelates with radioactive contaminants found in the circulation, interstitial fluid, and tissues. When Ca-DTPA is administered by inhalation within 24 hours of internal radioactive contamination, it can chelate transuranium elements. Expectoration is expected to decrease the amount of radioactive contaminant available for systemic absorption.

The effectiveness of chelation decreases with time after internal contamination because the transuranium elements become incorporated into the tissues. Chelation treatment should be given as soon as possible after known or suspected internal contamination with transuranium elements has occurred. (See DOSAGE AND ADMINISTRATION)

Pharmacokinetics

Plasma retention and urinary excretion data were obtained in 2 subjects that received 750 kBq of ^14C-DTPA. As shown in Figure 1, the radiolabeled DTPA was rapidly distributed throughout the extracellular fluid space and was cleared by glomerular filtration. The plasma retention up to 7 hours post dosing was expressed by the sum of three exponential components with average half-lives of 1.4 min, 14.5 min, and 94.4 min. The level of activity in the plasma was below the limit of detection 24 hours after injection. During the study, no detectable activity was exhaled or excreted in the feces. By 24 hours, cumulative urinary excretion was more than 99% of the injected dose.

Absorption

Ca-DTPA is poorly absorbed in the GI tract. In animal studies, after oral administration, absorption was approximately 5%. In a U.S. Registry of 18 patients who received a single inhaled or intravenous dose of 1 gram, urine data indicate that the inhaled product was absorbed and resulted in a comparable elimination of the radiocontaminant. One study of 2 human subjects that received Ca-DTPA with ^14C-DTPA by inhalation revealed approximately 20% absorption from the lungs. Human or animal bioavailability comparisons for Ca-DTPA are not available after administration by inhalation and intravenous injection. (See CLINICAL PHARMACOLOGY, Clinical Trials)

Distribution

Following intravenous administration, Ca-DTPA is rapidly distributed throughout the extracellular fluid space. No significant amount of Ca-DTPA penetrates into erythrocytes or other cells. No accumulation of Ca-DTPA in specific organs has been observed. There is little or no binding of the chelating agent by the renal parenchyma.

Metabolism

Ca-DTPA undergoes a minimal amount of metabolic change in the body.

Adverse Metabolic Effects

Studies in animals and humans showed that Ca-DTPA binds endogenous metals of the body (i.e., zinc (Zn), magnesium (Mg) and manganese (Mn)). In an animal study, high doses of Ca-DTPA led to the loss of zinc and manganese mainly from the small intestine, skeleton, pancreas, and testes. Dosing over several days resulted in mobilization or binding of endogenous metals in exchange for calcium and a consequent impairment of metal-controlled or activated systems. The rate and amount of endogenous metal depletion increased with split daily dosing and with the length of treatment. Depletion of these endogenous metals can interfere with necessary mitotic cellular processes. Over longer time periods, depletion of zinc due to Ca-DTPA therapy may result in transient inhibition of a metalloenzyme-δ-aminolevulinic acid dehydrase (ALAD) in the blood and suppressed hematopoiesis.

Elimination

Ca-DTPA is cleared from the plasma in the first few hours after dosing through urinary excretion by glomerular filtration. Renal tubular excretion has not been documented. In stool samples tested, only a very small amount of radioactivity (<3%) was detected.

Renal Impaired and/or Compromised Liver Function Patients

Adequate and well-controlled pharmacokinetic and pharmacodynamic studies in renally impaired and/or hepatically impaired patients were not identified in the literature. Both Ca-DTPA and its radioactive chelates are excreted by glomerular filtration. Impaired renal function may decrease their rates of elimination and increase the serum half-life of Ca-DTPA.

Clinical Trials

All clinical data has come from the treatment of individuals who were accidentally contaminated. Observational data were maintained in a U.S. Registry of individuals with internal radioactive contamination primarily from acute occupational contamination with plutonium, americium, and curium.

In 286 individuals, bioassays were available to measure urinary radioactivity elimination after chelation therapy. Of these 286 individuals, 18 had matched pre- and post-chelator urine radioactivity bioassay results available. Seventeen of these individuals received 1 gram of Ca-DTPA as the first dose. Of these, 9 individuals received the first dose by nebulization (1:1 Ca-DTPA and saline) and 8 received Ca-DTPA intravenously. The elimination of radiocontaminants was measured using the ratio of the urine radioactivity before treatment to the maximum urine radioactivity after treatment (the excretion enhancement factor, EEF). As shown in Table 1, after one dose, the mean EEF was 25.7. The descriptive results and variability for the intravenous, inhaled, and combined routes are considered to be similar.

Table 1 : Urine Excretion Enhancement Factor (EEF) of Transuranium Elements after an Initial Dose of 1g Ca-DTPA, N=17
Results | Intravenous | Inhaled | Combined Routes
Mean | 25.9 | 25.4 | 25.7
Median | 12.5 | 19.3 | 12.8
SD | 33.8 | 28.2 | 30.1
Range | 1.1-396.1 | 0.5-80.0 | 0.5-396.1

After initial treatment with Ca-DTPA, maintenance treatment was continued with 1 gram Zn-DTPA doses over a period of days, months or years, depending upon the extent of internal contamination and individual response to therapy. Most patients received a single dose of Ca-DTPA. The longest treatment duration was approximately 6.5 years. Similar increases in urinary radioactivity elimination following chelator administration were supported by data from the remaining 268 individuals in the U.S. Registry and from the literature.

INDICATIONS AND USAGE

Ca-DTPA is indicated for treatment of individuals with known or suspected internal contamination with plutonium, americium, or curium to increase the rates of elimination.

CONTRAINDICATIONS

None known.

WARNINGS

Ca-DTPA is associated with depletion of endogenous trace metals (e.g., zinc, magnesium, manganese). The magnitude of depletion increases with split daily dosing, with increasing dose, and with increased treatment duration. (See CLINICAL PHARMACOLOGY, Pharmacodynamics, Adverse Metabolic Effects). Only a single initial dose of Ca-DTPA is recommended. After the initial single dose of Ca-DTPA, if additional chelation therapy is indicated, it is recommended that therapy be continued with Zn-DTPA. (See Zn-DTPA labeling) If Zn-DTPA is not available, chelation therapy may continue with Ca-DTPA but mineral supplements containing zinc should be given concomitantly, as appropriate.

Ca-DTPA should be used with caution in individuals with severe hemochromatosis. Deaths have been reported in patients with severe hemochromatosis that received up to 4 times the recommended daily dose, for more than 1 day, by IM injection. Causal association with these events and drug has not been established. (See OVERDOSE).

Nebulized chelation therapy may be associated with exacerbation of asthma. Caution should be exercised when administering Ca-DTPA by the inhalation route. (See ADVERSE REACTIONS)

PRECAUTIONS

Information for Patients

Radioactive metals are known to be excreted in the urine, feces, and breast milk. In individuals with recent internal contamination with plutonium, americium, or curium, Ca-DTPA treatment increases excretion of radioactivity in the urine. Appropriate safety measures should be taken to minimize contamination of others. When possible, a toilet should be used instead of a urinal, and it should be flushed several times after each use. Spilled urine or feces should be cleaned up completely and patients should wash their hands thoroughly. If blood or urine comes in contact with clothing or linens, they should be washed separately. Patients should drink plenty of fluids and void frequently. If patients are coughing, any expectorant should be disposed of carefully. Swallowing the expectorant should be avoided if possible. Parents and child-care givers should take extra precaution in handling the urine, feces, and expectorants of children to avoid any additional exposure to either the care-giver or to the child. Nursing mothers should take extra precaution in disposing of breast milk. (See PRECAUTIONS, Nursing Mothers)

Laboratory Tests

Serum electrolytes and essential metals should be closely monitored during Ca-DTPA treatment. Mineral or vitamin plus mineral supplements that contain zinc should be given as appropriate. (See WARNINGS)

Drug-Drug Interactions

Adequate and well-controlled drug-drug interaction studies in humans were not identified in the literature. When an individual is contaminated with multiple radiocontaminants, or when the radiocontaminants are unknown, additional therapies may be needed (e.g., Prussian blue, potassium iodide).

Carcinogenesis, Mutagenesis, Impairment of Fertility

Studies with Ca-DTPA to evaluate carcinogenesis, mutagenesis, and impairment of fertility have not been performed. Data for Ca-DTPA effects on spermatogenesis are not available.

Teratogenic Effects

Pregnancy Category C

There are no human pregnancy outcome data from which to assess the risk of Ca-DTPA exposure on fetal development. Ca-DTPA is believed to be teratogenic based on animal data and because chelation therapy results in the depletion of body stores of zinc which is known to affect DNA and RNA synthesis in humans. There are no animal or human data evaluating the teratogenic effect of the administration of a single dose of Ca-DTPA. Based on its mechanism of action, the likelihood that a single dose or multiple doses of Ca-DTPA is teratogenic in humans cannot be ruled out. In mice, Ca-DTPA has been shown to be teratogenic and embryocidal following five daily injections of 720-2880 µmol Ca-DTPA/kg [2- 8 times the recommended daily human dose of 1 gram based on body surface area (BSA) adjusted dose] given during any period of gestation. The frequency of gross malformations (e.g., exencephaly, spina bifida, and cleft palate) increased with dose, with higher susceptibility in early and mid gestation. Five daily doses of 360 µmol Ca-DTPA/kg in mice, approximately equivalent to the recommended daily human dose (based on BSA) produced no harmful effects. Studies of 2 pregnant dogs given daily injections of 30 µmol Ca-DTPA/kg (approximately half the recommended daily human dose based on BSA) from implantation until parturition showed severe teratogenic effects (especially brain damage).

Multiple doses of Ca-DTPA could result in an increased risk for adverse reproductive outcomes and thus are not recommended during pregnancy. Therefore, treatment of pregnant women should begin and continue with Zn-DTPA, if available, except in cases of high internal radioactive contamination. In these cases, the risk of immediate and delayed radiation-induced toxicity to both the mother and the fetus should be considered in comparison to the risk of Ca-DTPA toxicity. Also, because Ca-DTPA is more effective than Zn-DTPA in the first 24 hours after internal contamination, it may be appropriate to use a single dose of Ca-DTPA with vitamin or mineral supplements that contain zinc as the initial treatment.

Nursing Mothers

Studies to determine if Ca-DTPA is excreted in breast milk have not been conducted. Radiocontaminants are known to be excreted in breast milk. Women with known or suspected internal contamination with radiocontaminants should not breast feed, whether or not they are receiving chelation therapy. Precautions should be taken when discarding breast milk. (See PRECAUTIONS, Information for Patients)

Pediatric Use

The safety and effectiveness of Ca-DTPA was established in the adult population and efficacy was extrapolated to the pediatric population for the intravenous route based on the comparability of pathophysiologic mechanisms. The dose is based on body size adjustment for an intravenous drug that is renally cleared. The safety and effectiveness of the nebulized route of administration has not been established in the pediatric population.

ADVERSE REACTIONS

In the U.S. Registry, a total of 646 individuals received at least one dose of either Ca-DTPA or Zn-DTPA. Of these, 632 received Ca-DTPA by one or more routes of administration. Three hundred and twenty-six individuals were dosed by inhalation, 293 by intravenous injection, and 60 by other or unknown routes of administration.

Of the individuals that received Ca-DTPA, 393/632 (62%) received one dose and 65 (10%) received two doses. The remaining 174 individuals received three or more doses. The largest number of Ca-DTPA doses to a single individual was 338 delivered over 6.5 years. Overall, the presence or absence of adverse events was recorded in 310/646 individuals. Of these 19 (6.1%) individuals reported at least one adverse event. The total number of recorded adverse events was 20. Of the 20 adverse events, 18 adverse events occurred after treatment with Ca-DTPA. Adverse events included headache, lightheadedness, chest pain, allergic reaction, dermatitis, metallic taste, nausea and diarrhea, and injection site reactions.

Cough and/or wheezing were experienced by 2 individuals receiving nebulized Ca-DTPA, one of whom had a history of asthma.

In the literature, prolonged treatment with Ca-DTPA resulted in depletion of zinc, magnesium, manganese and possibly metalloproteinases.(See WARNINGS)

OVERDOSAGE

In previous clinical studies, three deaths were reported in patients with severe hemochromatosis who were treated with daily IM Ca-DTPA dosed up to 4 gram per day to reduce iron stores. One patient became comatose and died after receiving a total of 14 gram Ca-DTPA, and the other two died after two weeks of daily treatment. Causal association with these events and the drug has not been established. (See WARNINGS)

DOSAGE AND ADMINISTRATION

Chelation treatment is most effective if administered within the first 24 hours after internal contamination and should be started as soon as possible after suspected or known internal contamination. However, even when treatment cannot be started right away, individuals should be given chelation treatment as soon as it becomes available. Chelation treatment is still effective even after time has elapsed following internal contamination however, the chelating effects of Ca-DTPA are greatest when radiocontaminants are still circulating or are in interstitial fluids. The effectiveness of chelation decreases with time following internal contamination as the radiocontaminants become sequestered in liver and bone.

Individuals should drink plenty of fluids and void frequently to promote dilution of the radioactive chelate in the urine and minimize radiation exposure directly to the bladder.

If internal contamination with radiocontaminants other than plutonium, americium, or curium, or unknown radiocontaminants is suspected, additional therapies may be needed (e.g., Prussian blue, potassium iodide).

Initial Dose

Adults and Adolescents

A single 1.0 gram initial dose of Ca-DTPA administered intravenously.

Pediatrics (less than 12 years of age)

A single initial dose of 14 mg/kg administered intravenously not exceed 1.0 gram.

Renally impaired patients

No dose adjustment is needed. However, renal impairment may reduce the rate at which chelators remove radiocontaminants from the body. In heavily contaminated patients with renal impairment, dialysis may be used to increase the rate of elimination. High efficiency high flux dialysis is recommended. Because dialysis fluid will become radioactive, radiation precautions must be taken to protect personnel, other patients, and the general public. If Ca-DTPA is not available, proceed with treatment with Zn-DTPA as initial therapy.

Maintenance Treatment

AFTER THE INITIAL DOSE, ON THE NEXT DAY, IF ADDITIONAL CHELATION THERAPY IS INDICATED, IT IS PREFERABLE TO SWITCH TO ZN-DTPA, IF AVAILABLE (SEE ZN-DTPA LABELING) DUE TO THE SAFETY CONCERNS ASSOCIATED WITH PROLONGED CA-DTPA USE. IF ZN-DTPA IS NOT AVAILABLE, TREATMENT MAY CONTINUE WITH CA-DTPA, HOWEVER MINERAL SUPPLEMENTS CONTAINING ZINC SHOULD BE GIVEN CONCOMITANTLY, AS APPROPRIATE.

Adults and Adolescents

The recommended maintenance dose of Ca-DTPA is 1.0 gram once a day administered intravenously.

Pediatrics (less than 12 years of age)

The recommended maintenance dose of Ca-DTPA is 14 mg/kg once a day administered intravenously. The maximum daily dose should not exceed 1.0 gram per day.

Renally impaired patients

No dose adjustment is needed.

The duration of chelation treatment depends on the amount of internal contamination and individual response to treatment. (See Monitoring)

Methods of Administration

Intravenous administration of Ca-DTPA is recommended and should be used if the route of internal contamination is not known or if multiple routes of internal contamination are likely. Ca-DTPA solution (1 gram in 5 mL) should be administered either with a slow intravenous push over a period of 3-4 minutes or by intravenous infusion diluted in 100-250 mL of 5% dextrose in water (D5W), Ringers Lactate, or Normal Saline.

In individuals whose internal contamination is only by inhalation within the preceding 24 hours, Ca-DTPA can be administered by nebulized inhalation as an alternative route of administration. Ca-DTPA should be diluted for nebulization at a 1:1 ratio with sterile water or saline. After nebulization, individuals should be encouraged to avoid swallowing any expectorant. Some individuals may experience respiratory adverse events after inhalation therapy. (See WARNINGS) The safety and effectiveness of the nebulized route of administration has not been established in the pediatric population.

The safety and effectiveness of the intramuscular route of injection have not been established. (See OVERDOSE)

Handling

OPC ampoule: to open, turn so that the point faces upward and break off the neck with a downward movement.

Parenteral drug products should be inspected visually for particulate matter and discoloration prior to administration, whenever solution and container permit. The product may be filtered using a sterile filter if particles are seen subsequent to opening of the ampoule.

Monitoring

When possible, obtain baseline blood and urine samples (CBC with differential, BUN, serum chemistries and electrolytes, urinalysis, and blood and urine radioassays) before initiating treatment.

Ca-DTPA must be given with very careful monitoring of serum zinc and complete blood counts. When appropriate, vitamin or mineral supplements that contain zinc should be administered. (See WARNINGS)

To establish an elimination curve, a quantitative baseline estimate of the total internalized transuranium element(s) and measures of elimination of radioactivity should be obtained by appropriate whole-body counting, by bioassay (e.g., biodosimetry), or fecal/urine sample whenever possible.

During Treatment

- Measure the radioactivity in blood, urine, and fecal samples weekly to monitor the radioactive contaminant elimination rate.
- Monitor CBC with differential, BUN, serum chemistries and electrolytes, and urinalysis regularly. If the individual is receiving more than one dose of Ca-DTPA, these laboratory tests should be very carefully monitored and consider mineral supplementation as appropriate. (See CLINICAL PHARMACOLOGY, Pharmacodynamics, Adverse Metabolic Effects)
- Record any adverse events from Ca-DTPA.

HOW SUPPLIED

Ca-DTPA is supplied as a sterile solution in 5 mL single-use clear glass ampoules at a concentration of 200 mg/mL for intravenous use. Each ampoule contains the equivalent of 1000 mg of pentetate calcium trisodium.

NDC 52919-001-03, 5 mL single-use ampoules, package of 10.

Storage

Store between 15 - 30°C (59 - 86°F).

COLLECTION OF PATIENT TREATMENT DATA

To develop long-term response data and information on the risk of developing late malignancy detailed information on patient treatment should be provided to the manufacturer (see Patient Treatment Data Form. In the case you need additional forms, please use the enclosed form as a template or see the following website: www.ca-dtpa.com). These data should include a record of the radioactive body burden and bioassay results at defined time intervals, a description of measurement methods to facilitate analysis of data, and adverse events.

Questions regarding the use of Ca-DTPA for the treatment of internal contamination with transuranium elements may be referred to:

hameln pharmaceuticals gmbh
Langes Feld 13
31789 Hameln, Germany
Tel.: +49-5151-581-0
Fax.: +49-5151-581-258
e-mail: welcome@hm-ph.com

contact person: Dr. Mathias Dewald
Tel.: +49-5151-581-214
Fax.: +49-5151-581-581
e-mail: m.dewald@hm-ph.com

hameln
pharmaceuticals

44641/19/05